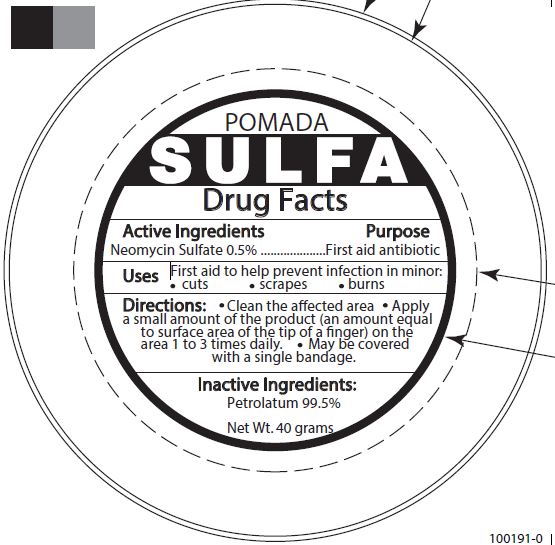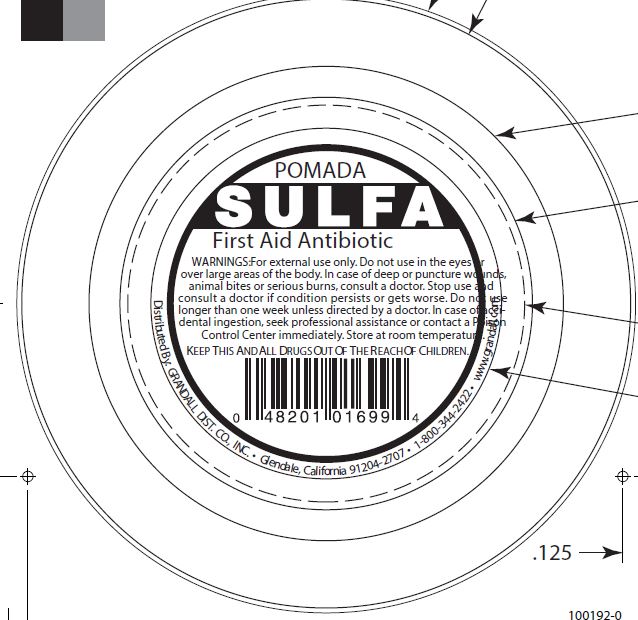 DRUG LABEL: POMADA SULFA FIRST AID ANTIBIOTIC
NDC: 48201-104 | Form: OINTMENT
Manufacturer: GRANDALL DISTRIBUTING, LLC
Category: otc | Type: HUMAN OTC DRUG LABEL
Date: 20251028

ACTIVE INGREDIENTS: NEOMYCIN SULFATE 0.5 g/100 g
INACTIVE INGREDIENTS: PETROLATUM 99.5 g/100 g

Grandall (as PLD) - POMADA SULFA FIRST AID ANTIBIOTIC (48201-104)

ACTIVE INGREDIENT

Neomycin Sulfate 0.5%

PURPOSE

FIRST AID ANTIBIOTIC

INDICATIONS

First aid to help prevent infection in minor

- cuts
- scrapes
- burns

WARNINGS

For external use only. Do not use in the eyes or over large areas of the body. In case of deep or puncture wounds, animal bites or serious burns, consult a doctor. Stop use and consult a doctor if condition persists or gets worse. Do not use longer than one week unless directed by a doctor. In case of accidental ingestion, seek professional assistance or contact a Poison Control Center immediately. Store at room temperature.

KEEP OUT OF REACH OF CHILDREN

KEEP THIS AND ALL DRUGS OUT OF THE REACH OF CHILDREN.

DIRECTIONS

- Clean the affected area.
- Apply a small amount of the product (an amount equal to surface area of the tip of a finger) on the area 1 to 3 times daily.
- May be covered with a single bandage.

INACTIVE INGREDIENTS

PETROLATUM 99.5%